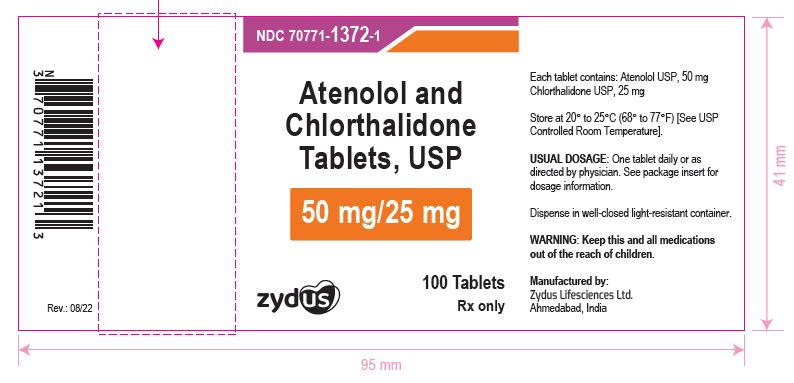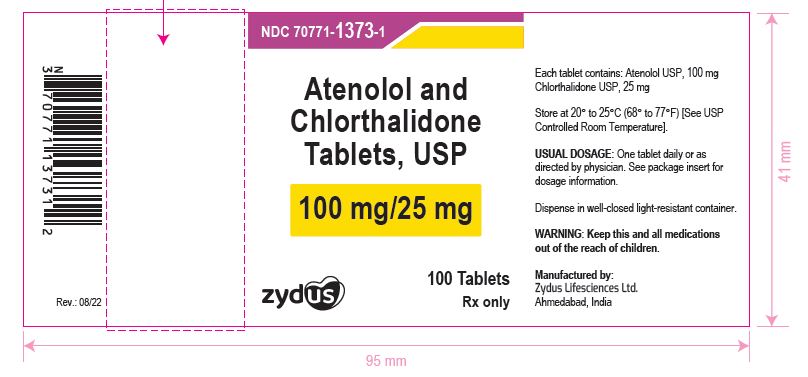 DRUG LABEL: Atenolol and Chlorthalidone
NDC: 70771-1372 | Form: TABLET
Manufacturer: Zydus Lifesciences Limited
Category: prescription | Type: HUMAN PRESCRIPTION DRUG LABEL
Date: 20241125

ACTIVE INGREDIENTS: ATENOLOL 50 mg/1 1; CHLORTHALIDONE 25 mg/1 1
INACTIVE INGREDIENTS: ANHYDROUS CITRIC ACID; CROSCARMELLOSE SODIUM; MAGNESIUM STEARATE; SILICON DIOXIDE; STARCH, CORN

Atenolol and Chlorthalidone Tablets, USP

PACKAGE LABEL.PRINCIPAL DISPLAY PANEL

NDC 70771-1372-1

Atenolol and Chlorthalidone Tablets, USP 50 mg/25 mg

Rx only

100 Tablets

NDC 70771-1373-1

Atenolol and Chlorthalidone Tablets, USP 100 mg/25 mg

Rx only

100 Tablets